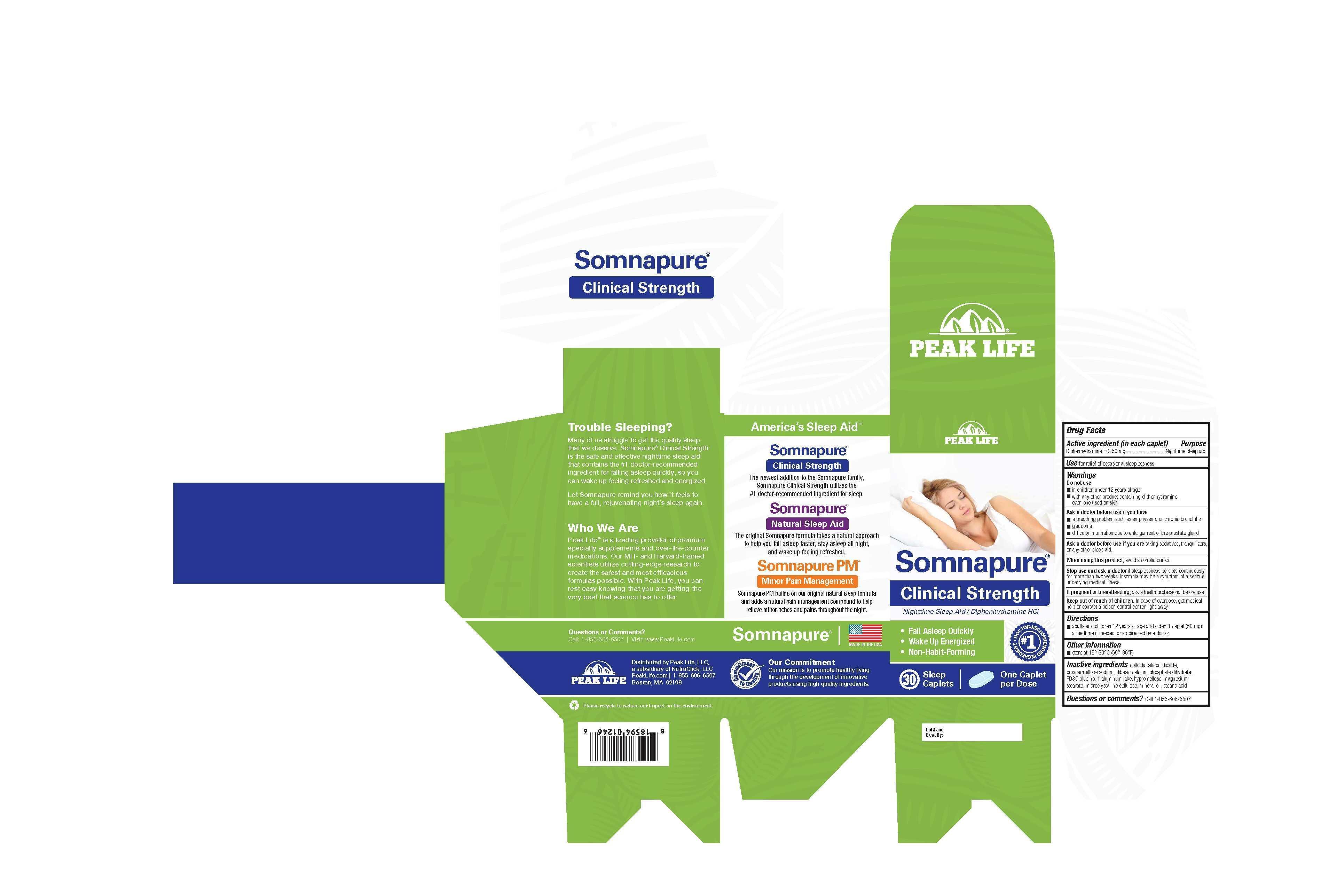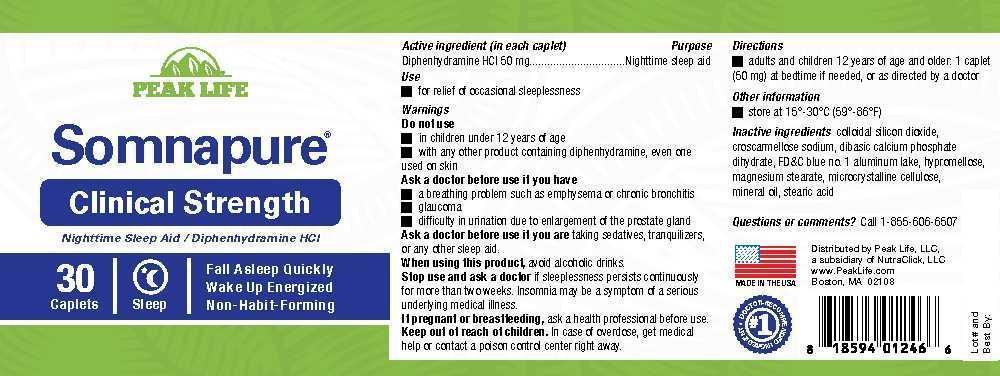 DRUG LABEL: Somnapure
NDC: 69721-002 | Form: TABLET, COATED
Manufacturer: NutraClick, LLC
Category: otc | Type: HUMAN OTC DRUG LABEL
Date: 20150526

ACTIVE INGREDIENTS: DIPHENHYDRAMINE HYDROCHLORIDE 50 mg/1 1
INACTIVE INGREDIENTS: COLLOIDAL SILICON DIOXIDE; CROSCARMELLOSE SODIUM; DIBASIC CALCIUM PHOSPHATE DIHYDRATE; FD&C BLUE NO. 1; HYPROMELLOSES; MAGNESIUM STEARATE; CELLULOSE, MICROCRYSTALLINE; MINERAL OIL; STEARIC ACID

Somnapure Clinical Strength

Drug Facts

Active ingredient (in each caplet)

Diphenhydramine HCl 50 mg

Purpose

Nighttime sleep aid

INDICATIONS AND USAGE

Use for relief of occasional sleeplessness

Warnings

Do not use

- in children under 12 years of age
- with any other product containing diphenhydramine, even one used on skin

Ask a doctor before use if you have

- a breathing problem such as emphysema or chronic bronchitis
- glaucoma
- difficulty in urination due to enlargement of the prostate gland

Ask a doctor before use if you are taking sedatives, tranquilizers, or any other sleep aid.

When using this product, avoid alcoholic drinks.

Stop use and ask a doctor if sleeplessness persists continuously for more than two weeks. Insomnia may be a symptom of a serious underlying medical illness.

PREGNANCY OR BREAST FEEDING

If pregnant or breastfeeding, ask a health professional before use.

Keep out of reach of children. In case of overdose, get medical help or contact a poison control center right away.

Directions

- adults and children 12 years of age and older: 1 caplet (50 mg) at bedtime if needed, or as directed by a doctor

Other information

- store at 15°-30°C (59°-86°F)

INACTIVE INGREDIENT

Inactive ingredients collodial silicon dioxide, croscarmellose sodium, dibasic calcium phosphate dihydrate, FD&C blue no. 1 aluminum lake, hypromellose, magnesium stearate, microcrystalline cellulose, mineral oil, stearic acid

Questions of comments? Call 1-855-606-6507

PACKAGE LABEL

Peak Life

Somnapure® Clinical Strength

Nighttime Sleep Aid / Diphenhydramine HCL

- Fall Asleep Quickly
- Wake Up Energized
- Non-Habit-Forming

#1 Doctor-Recommended Ingredient

30 Sleep Caplets

One Caplet per Dose

Distributed by Peak Life, LLC,

a subsidiary of NutraClick, LLC

PeakLife.com / 1-855-606-6507

Boston, MA 02108